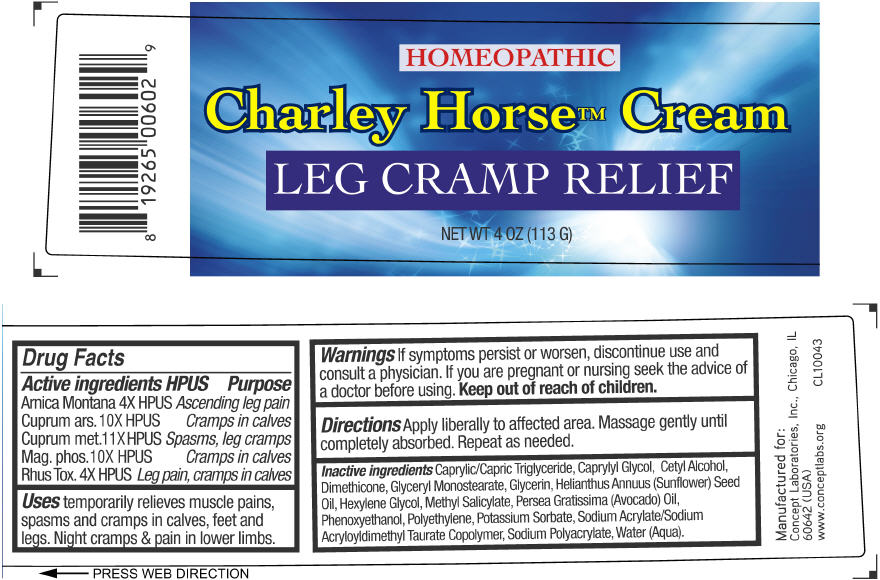 DRUG LABEL: Charley Horse
NDC: 64058-159 | Form: CREAM
Manufacturer: Concept Laboratories, Inc.
Category: homeopathic | Type: HUMAN OTC DRUG LABEL
Date: 20160216

ACTIVE INGREDIENTS: ARNICA MONTANA 4 [hp_X]/113 g; CUPRIC ARSENITE 10 [hp_X]/113 g; COPPER 11 [hp_X]/113 g; MAGNESIUM PHOSPHATE, DIBASIC TRIHYDRATE 10 [hp_X]/113 g; TOXICODENDRON PUBESCENS LEAF 4 [hp_X]/113 g
INACTIVE INGREDIENTS: MEDIUM-CHAIN TRIGLYCERIDES; Caprylyl Glycol; Cetyl Alcohol; Dimethicone; Glyceryl Monostearate; Glycerin; SUNFLOWER OIL; Hexylene Glycol; Methyl Salicylate; AVOCADO OIL; Phenoxyethanol; HIGH DENSITY POLYETHYLENE; Potassium Sorbate; Sodium Acrylate; Water

Charley Horse™ Cream

Drug Facts

ACTIVE INGREDIENT

Active ingredients HPUS | Purpose
Arnica Montana 4X HPUS | Ascending leg pain
Cuprum ars. 10X HPUS | Cramps in calves
Cuprum met. 11X HPUS | Spasms, leg cramps
Mag. phos. 10X HPUS | Cramps in calves
Rhus Tox. 4X HPUS | Leg pain, cramps in calves

Uses

temporarily relieves muscle pains, spasms and cramps in calves, feet and legs. Night cramps & pain in lower limbs.

Warnings

KEEP OUT OF REACH OF CHILDREN

If symptoms persist or worsen, discontinue use and consult a physician. If you are pregnant or nursing seek the advice of a doctor before using. Keep out of reach of children.

Directions

Apply liberally to affected area. Massage gently until completely absorbed. Repeat as needed.

Inactive ingredients

Caprylic/Capric/Triglyceride, Caprylyl Glycol, Cetyl Alcohol, Dimethicone, Glyceryl Monostearate, Gycerin, Helianthus Annuus (Sunflower) Seed Oil, Hexylene Glycol, Methyl Salicylate, Persea Gratissima (Avocado) Oil, Phenoxyethanol, Polyethylene, Potassium Sorbate, Sodium Acrylate/Sodium Acryloyl Dimethyl Taurate Copolymer, Sodium Polyacrylate, Water (Aqua).

Manufactured for: Concept Laboratories, Inc., Chicago, IL 60642 (USA)
www.conceptlabs.org
CL10043

PRINCIPAL DISPLAY PANEL - 113 G Jar Label

HOMEOPATHIC
Charley Horse™ Cream
Leg Cramp Relief
NET WT 4 OZ (113 G)